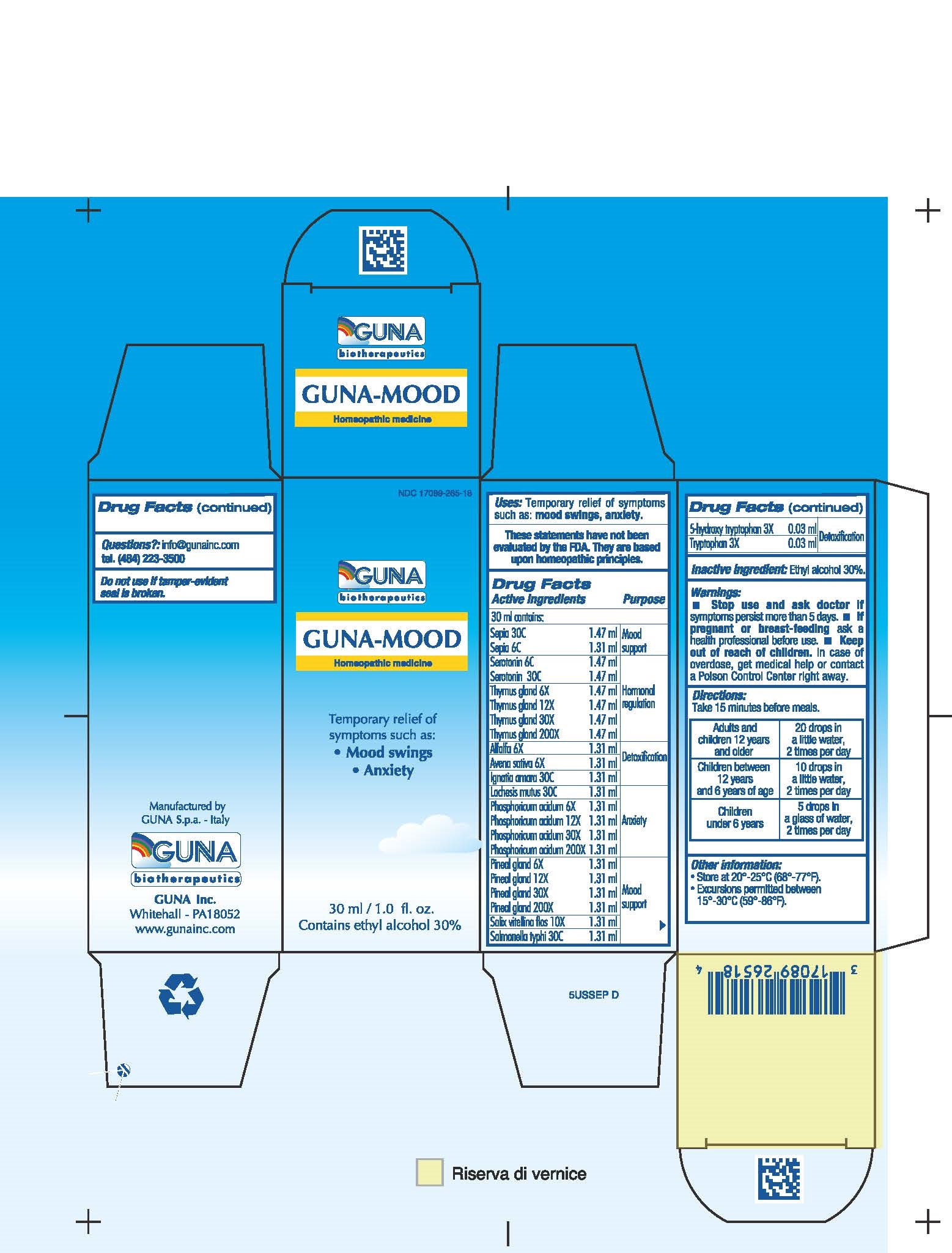 DRUG LABEL: GUNA-MOOD
NDC: 17089-265 | Form: SOLUTION/ DROPS
Manufacturer: Guna spa
Category: homeopathic | Type: HUMAN OTC DRUG LABEL
Date: 20221114

ACTIVE INGREDIENTS: 5-HYDROXYTRYPTOPHAN, DL- 3 [hp_X]/30 mL; ALFALFA 6 [hp_X]/30 mL; AVENA SATIVA FLOWERING TOP 6 [hp_X]/30 mL; STRYCHNOS IGNATII SEED 30 [hp_C]/30 mL; LACHESIS MUTA VENOM 30 [hp_C]/30 mL; PHOSPHORIC ACID 200 [hp_X]/30 mL; SUS SCROFA PINEAL GLAND 200 [hp_X]/30 mL; SALIX ALBA BARK 10 [hp_X]/30 mL; SALMONELLA ENTERICA SUBSP. ENTERICA SEROVAR TYPHI 30 [hp_C]/30 mL; SEPIA OFFICINALIS JUICE 30 [hp_C]/30 mL; SEROTONIN 30 [hp_C]/30 mL; SUS SCROFA THYMUS 200 [hp_X]/30 mL; TRYPTOPHAN 3 [hp_X]/30 mL
INACTIVE INGREDIENTS: ALCOHOL 9 mL/30 mL

GUNA-MOOD

ACTIVE INGREDIENTS/PURPOSE

5-HYDROXY TRYPTOPHAN 3X DETOXIFICATION
ALFALFA 6X DETOXIFICATION
AVENA SATIVA 6X DETOXIFICATION
IGNATIA AMARA 30C ANXIETY
LACHESIS MUTUS 30C ANXIETY
PHOSPHORICUM ACIDUM 6X 12X 30X 200X ANXIETY
PINEAL GLAND 6X 12X 30X 200X HORMONAL REGULATION
SALIX VITELLINA FLOS 10X MOOD SUPPORT
SALMONELLA TYPHI 30C MOOD SUPPORT
SEPIA 6C 30C MOOD SUPPORT
SEROTONIN 6C 30C HORMONAL REGULATION
THYMUS GLAND 6X 12X 30X 200X HORMONAL REGULATION
TRYPTOPHAN 3X DETOXIFICATION

USES

Temporary relief of symptoms such as:

- Mood swings
- Anxiety

WARNINGS

- Stop use and ask doctor if symptoms persist more than 5 days.
- If pregnant or breast-feeding ask a health professional before use.
- Keep out of reach of children. In case of overdose, get medical help or contact a Poison Control Center right away.
- Contains ethyl alcohol 30%

PREGNANCY

If pregnant or breast-feeding ask a doctor before use

WARNINGS

Keep out of reach of children

DIRECTIONS

Adults and children 12 years and older 20 drops in a little water 2 times per day
Children between 12 years and 6 years of age 10 drops in a little water 2 times per day
Children under 6 years 5 drops in a glass of water 2 times per day

QUESTIONS

Questions?: info@gunainc.com
Tel. (484) 223-3500

INDICATIONS AND USAGE

Take 15 minutes before meals

Inactive ingredient: Ethyl alcohol 30%.